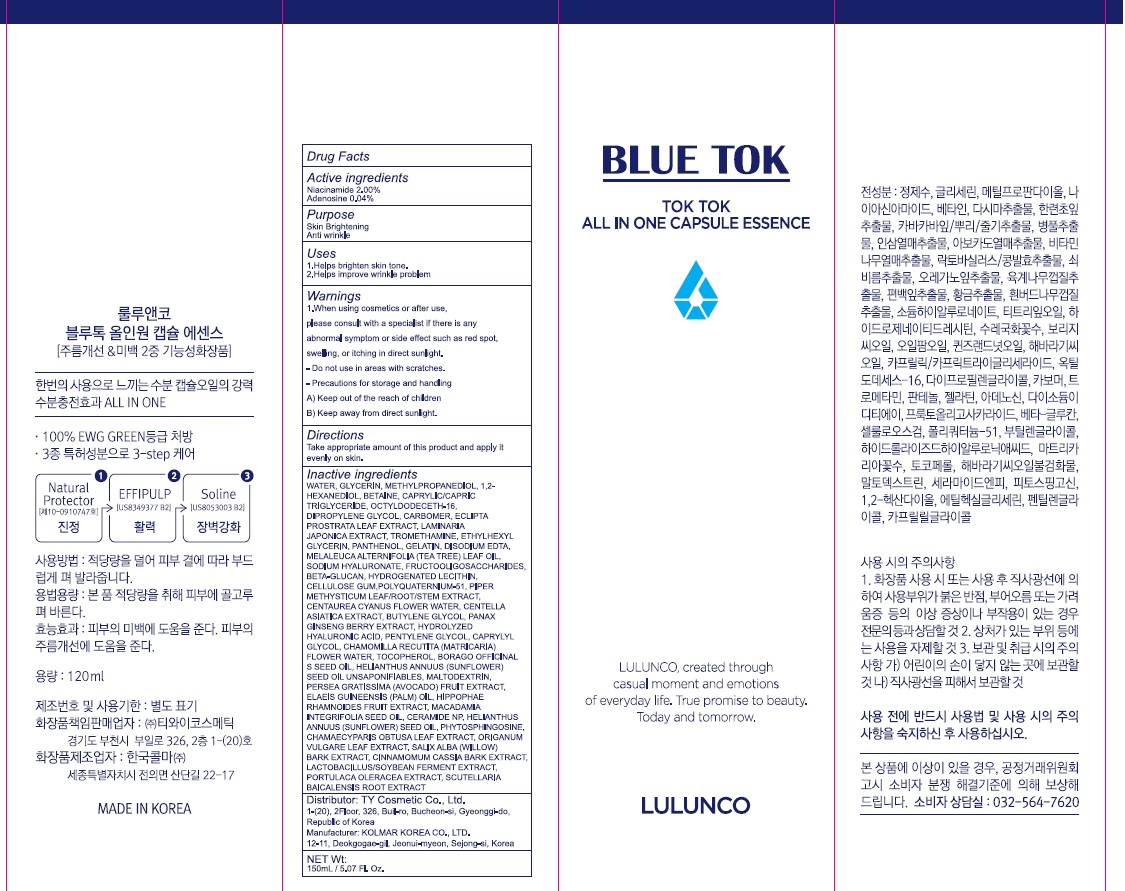 DRUG LABEL: BLUE TOK TOK TOK ALL IN ONE CAPSULE ESSENCE
NDC: 73523-010 | Form: LIQUID
Manufacturer: Ty Cosmetic Co.,ltd
Category: otc | Type: HUMAN OTC DRUG LABEL
Date: 20191224

ACTIVE INGREDIENTS: Niacinamide 3.0 g/150 mL; Adenosine 0.06 g/150 mL
INACTIVE INGREDIENTS: WATER; GLYCERIN

ACTIVE INGREDIENT

Active Ingredient: Niacinamide 2.00%, Adenosine 0.04%

INACTIVE INGREDIENT

Inactive Ingredients:

WATER, GLYCERIN, METHYLPROPANEDIOL, 1,2-HEXANEDIOL, BETAINE, CAPRYLIC/CAPRIC TRIGLYCERIDE, OCTYLDODECETH-16, DIPROPYLENE GLYCOL, CARBOMER, ECLIPTA PROSTRATA LEAF EXTRACT, LAMINARIA JAPONICA EXTRACT, TROMETHAMINE, ETHYLHEXYLGLYCERIN, PANTHENOL, GELATIN, DISODIUM EDTA, MELALEUCA ALTERNIFOLIA (TEA TREE) LEAF OIL, SODIUM HYALURONATE, FRUCTOOLIGOSACCHARIDES, BETA-GLUCAN, HYDROGENATED LECITHIN, CELLULOSE GUM, POLYQUATERNIUM-51, PIPER METHYSTICUM LEAF/ROOT/STEM EXTRACT, CENTAUREA CYANUS FLOWER WATER, CENTELLA ASIATICA EXTRACT, BUTYLENE GLYCOL, PANAX GINSENG BERRY EXTRACT, HYDROLYZED HYALURONIC ACID, PENTYLENE GLYCOL, CAPRYLYL GLYCOL, CHAMOMILLA RECUTITA (MATRICARIA) FLOWER WATER, TOCOPHEROL, BORAGO OFFICINALIS SEED OIL, HELIANTHUS ANNUUS (SUNFLOWER) SEED OIL UNSAPONIFIABLES, MALTODEXTRIN, PERSEA GRATISSIMA (AVOCADO) FRUIT EXTRACT, ELAEIS GUINEENSIS (PALM) OIL, HIPPOPHAE RHAMNOIDES FRUIT EXTRACT, MACADAMIA INTEGRIFOLIA SEED OIL, CERAMIDE NP, HELIANTHUS ANNUUS (SUNFLOWER) SEED OIL, PHYTOSPHINGOSINE, CHAMAECYPARIS OBTUSA LEAF EXTRACT, ORIGANUM VULGARE LEAF EXTRACT, SALIX ALBA (WILLOW) BARK EXTRACT, CINNAMOMUM CASSIA BARK EXTRACT, LACTOBACILLUS/SOYBEAN FERMENT EXTRACT, PORTULACA OLERACEA EXTRACT, SCUTELLARIA BAICALENSIS ROOT EXTRACT

PURPOSE

Purpose: Skin Brightening, Anti wrinkle

WARNINGS

1. When using cosmetics or after use, please consult with a specialist if there is any abnormal symptom or side effect such as red spot, swelling, or itching in direct sunlight.
2. Do not use in areas with scratches.
3. Precautions for storage and handling
A) Keep out of the reach of children
B) Keep away from direct sunlight.

KEEP OUT OF REACH OF CHILDREN

USES

1. Helps brighten skin tone.
2. Helps improve wrinkle problem

Directions

Take appropriate amount of this product and apply it evenly on skin.